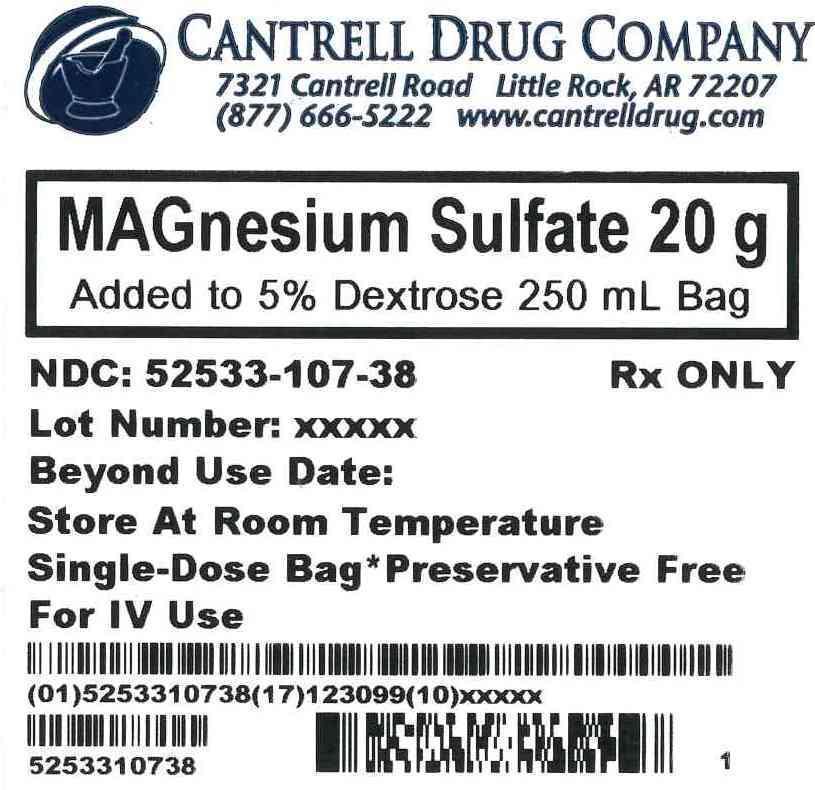 DRUG LABEL: Magnesium Sulfate
NDC: 52533-107 | Form: INJECTION, SOLUTION
Manufacturer: Cantrell Drug Company
Category: prescription | Type: HUMAN PRESCRIPTION DRUG LABEL
Date: 20121121

ACTIVE INGREDIENTS: MAGNESIUM SULFATE 20 g/250 mL
INACTIVE INGREDIENTS: Dextrose 12.5 g/250 mL; Water

Magnesium Sulfate 20 g Added to 5% Dextrose 250 mL Bag